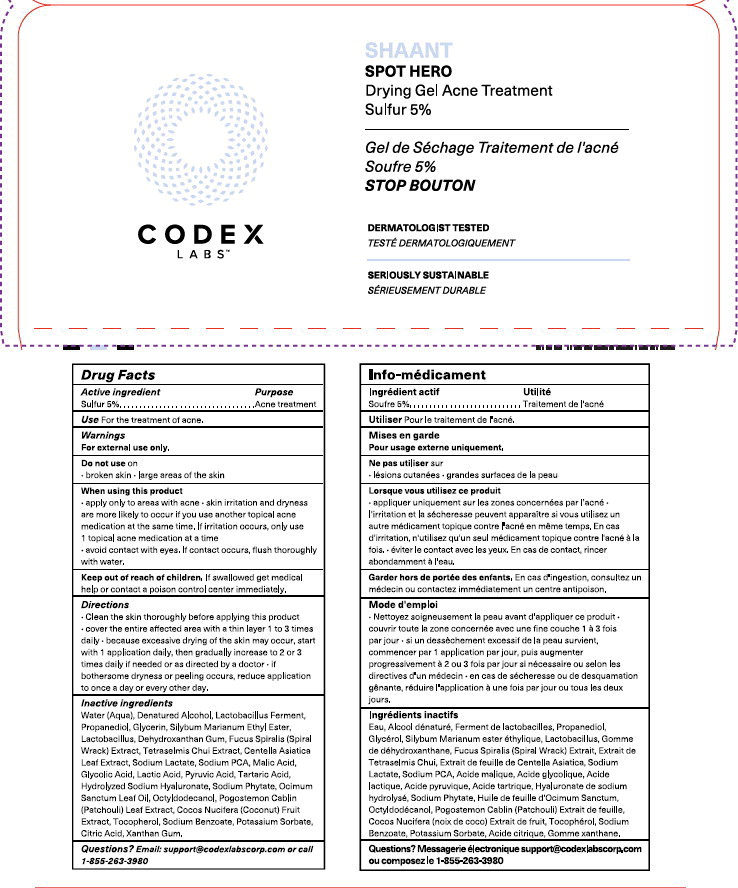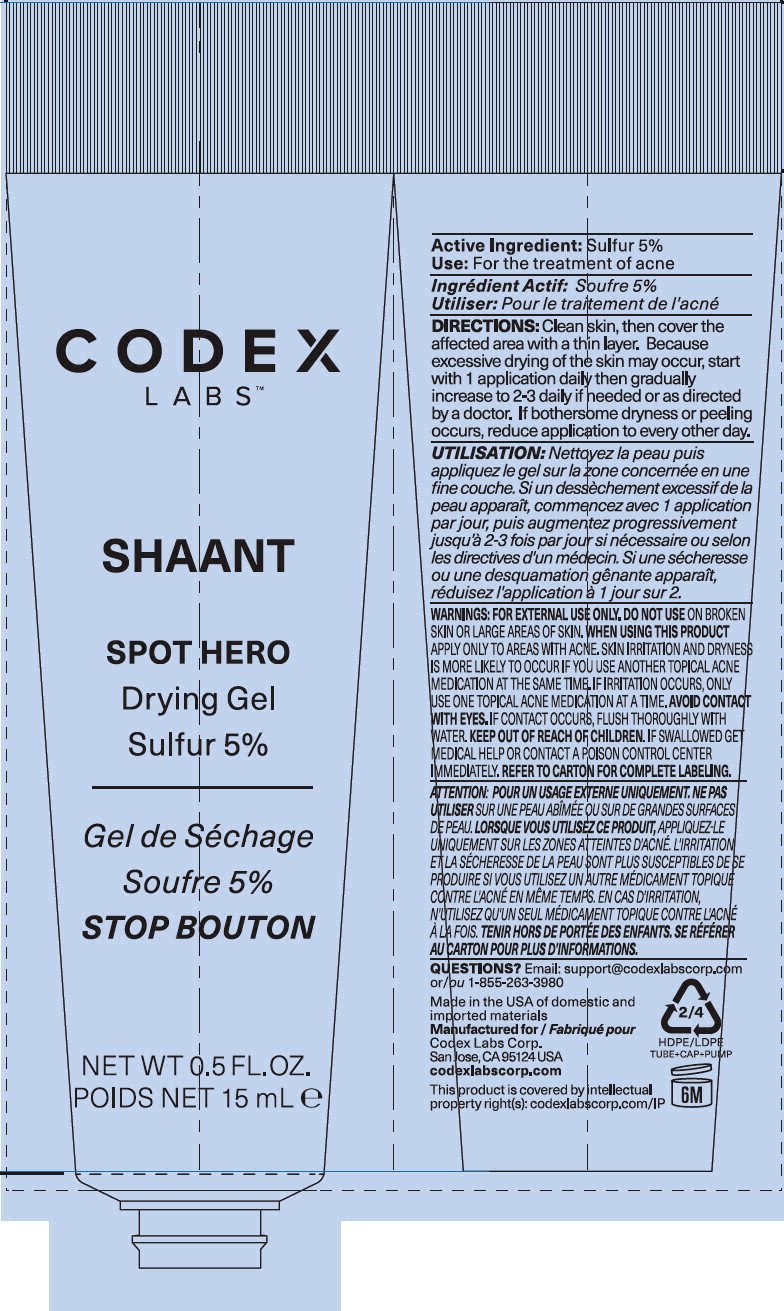 DRUG LABEL: Shaant Spot Hero Drying Acne Treatment
NDC: 83196-690 | Form: GEL
Manufacturer: Codex Labs Corporation
Category: otc | Type: HUMAN OTC DRUG LABEL
Date: 20251121

ACTIVE INGREDIENTS: Sulfur 50 mg/1 mL
INACTIVE INGREDIENTS: WATER; ALCOHOL; BETULA PUBESCENS BARK; PROPANEDIOL; GLYCERIN; DEHYDROXANTHAN GUM; FUCUS SPIRALIS; TETRASELMIS CHUI; CENTELLA ASIATICA LEAF; SODIUM LACTATE; SODIUM PYRROLIDONE CARBOXYLATE; MALIC ACID; GLYCOLIC ACID; LACTIC ACID, UNSPECIFIED FORM; HYALURONATE SODIUM; PYRUVIC ACID; TARTARIC ACID; PHYTATE SODIUM; OCIMUM TENUIFLORUM LEAF OIL; OCTYLDODECANOL; POGOSTEMON CABLIN TOP; COCONUT; TOCOPHEROL; SODIUM BENZOATE; POTASSIUM SORBATE; CITRIC ACID MONOHYDRATE; XANTHAN GUM; ZOSTERA MARINA WHOLE; LACTOBACILLUS ACIDOPHILUS; SILYBUM MARIANUM ETHYL ESTER

Drug Facts

Active ingredient

Sulfur 5%

Purpose

Acne treatment

Use

For the treatment of acne.

Warnings

For external use only.

Do not use on

- broken skin
- large areas of the skin

When using this product

- apply only to areas with acne
- skin irritation and dryness are more likely to occur if you use another topical acne medication at the same time. If irritation occurs, only use 1 topical acne medication at a time
- avoid contact with eyes. If contact occurs, flush thoroughly with water.

Keep out of reach of children.

If swallowed get medical help or contact a poison control center immediately.

Directions

- Clean the skin thoroughly before applying this product
- cover the entire affected area with a thin layer 1 to 3 times daily
- because excessive drying of the skin may occur, start with 1 application daily, then gradually increase to 2 or 3 times daily if needed or as directed by a doctor
- if bothersome dryness or peeling occurs, reduce application to once a day or every other day.

Inactive ingredients

Water (Aqua), Denatured Alcohol, Lactobacillus Ferment, Propanediol, Glycerin, Silybum Marianum Ethyl Ester, Lactobacillus, Dehydroxanthan Gum, Fucus Spiralis (Spiral Wrack) Extract, Tetraselmis Chui Extract, Centella Asiatica Leaf Extract, Sodium Lactate, Sodium PCA, Malic Acid, Glycolic Acid, Lactic Acid, Pyruvic Acid, Tartaric Acid, Hydrolyzed Sodium Hyaluronate, Sodium Phytate, Ocimum Sanctum Leaf Oil, Octyldodecanol, Pogostemon Cablin (Patchouli) Leaf Extract, Cocos Nucifera (Coconut) Fruit Extract, Tocopherol, Sodium Benzoate, Potassium Sorbate, Citric Acid, Xanthan Gum.

Questions?

Email support@codexlabscorp.com or call 1-855-263-3980

Info-médicament

Ingrédient actif

Soufre 5%

Utilité

Traitement de l'acné

Utiliser

Pour le traitement de l'acné.

Mises en garde

Pour usage externe uniquement.

DO NOT USE

Ne pas utiliser sur

- lésions cutanées
- grandes surfaces de la peau

Lorsque vous utilisez ce produit

- appliquer uniquement sur les zones concernées par l'acné
- l'irritation et la sécheresse peuvent apparaître si vous utilisez un autre médicament topique contre l'acné en même temps. En cas d'irritation, n'utilisez qu'un seul médicament topique contre l'acné à la fois.
- éviter le contact avec les yeux. En cas de contact, rincer abondamment à l'eau.

Garder hors de portée des enfants.

En cas d'ingestion, consultez un médecin ou contactez immédiatement un centre antipoison.

Mode d'emploi

- Nettoyez soigneusement la peau avant d'appliquer ce produit
- couvrir toute la zone concernée avec une fine couche 1 à 3 fois par jour
- si un dessèchement excessif de la peau survient, commencer par 1 application par jour, puis augmenter progressivement à 2 ou 3 fois par jour si nécessaire ou selon les directives d'un médecin
- en cas de sécheresse ou de desquamation gênante, réduire l'application à une fois par jour ou tous les deux jours.

Ingrédients inactifs

Eau, Alcool dénaturé, Ferment de lactobacilles, Propanediol, Glycérol, Silybum Marianum ester éthylique, Lactobacillus, Gomme de déhydroxanthane, Fucus Spiralis (Spiral Wrack) Extrait, Extrait de Tetraselmis Chui, Extrait de feuille de Centella Asiatica, Sodium Lactate, Sodium PCA, Acide malique, Acide glycolique, Acide lactique, Acide pyruvique, Acide tartrique, Hyaluronate de sodium hydrolysé, Sodium Phytate, Huile de feuille d'Ocimum Sanctum, Octyldodécanol, Pogostemon Cablin (Patchouli) Extrait de feuille, Cocos Nucifera (noix de coco) Extrait de fruit, Tocophérol, Sodium Benzoate, Potassium Sorbate, Acide citrique, Gomme xanthane.

Questions?

Messagerie électronique support@codexlabscorp.com ou composez le 1-855-263-3980

Made in the USA of domestic and imported materials

Manufactured for

Fabriqué par

Codex Labs Corp.

San Jose, CA 95124 USA

codexlabscorp.com

This product is covered by patent(s) or other intellectual

property right(s); see codexlabscorp.com/IP for more details.

Principal Display Panel – 15 mL Carton Label

CODEX
LABS™

SHAANT

SPOT HERO

Drying Gel Acne Treatment

Sulfur 5%

Gel de Séchage Traitement de l'acné

Soufre 5%

STOP BOUTON

DERMATOLOGIST TESTED

TESTÉ DERMATOLOGIQUEMENT

SERIOUSLY SUSTAINABLE

SÉRIEUSEMENT DURABLE

Principal Display Panel – 15 mL Tube Label

CODEX
LABS™

SHAANT

SPOT HERO

Drying Gel

Sulfur 5%

Gel de Séchage

Soufre 5%

STOP BOUTON

NET WT 0.5 FL. OZ. / POIDS NET 15 mL e